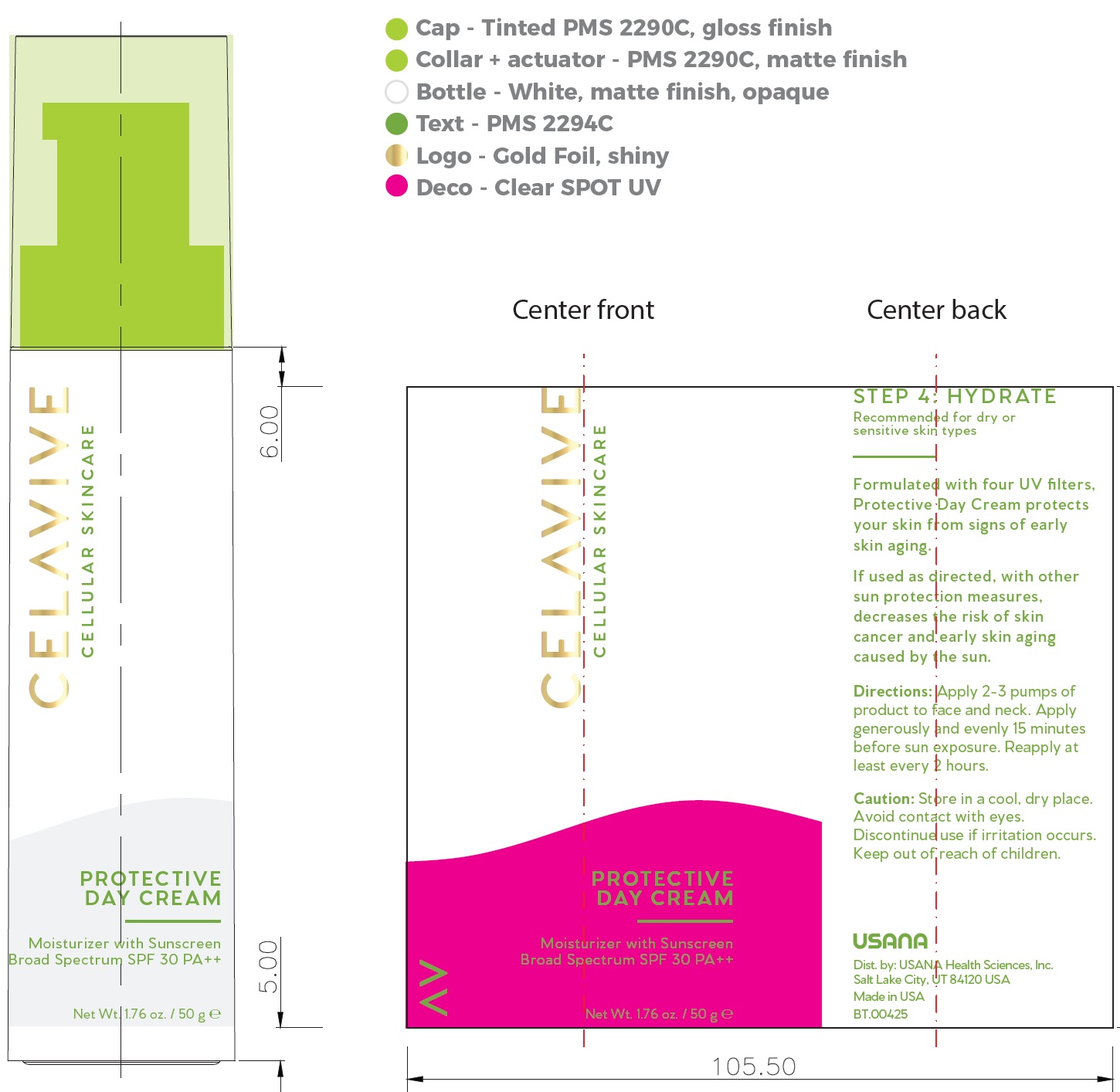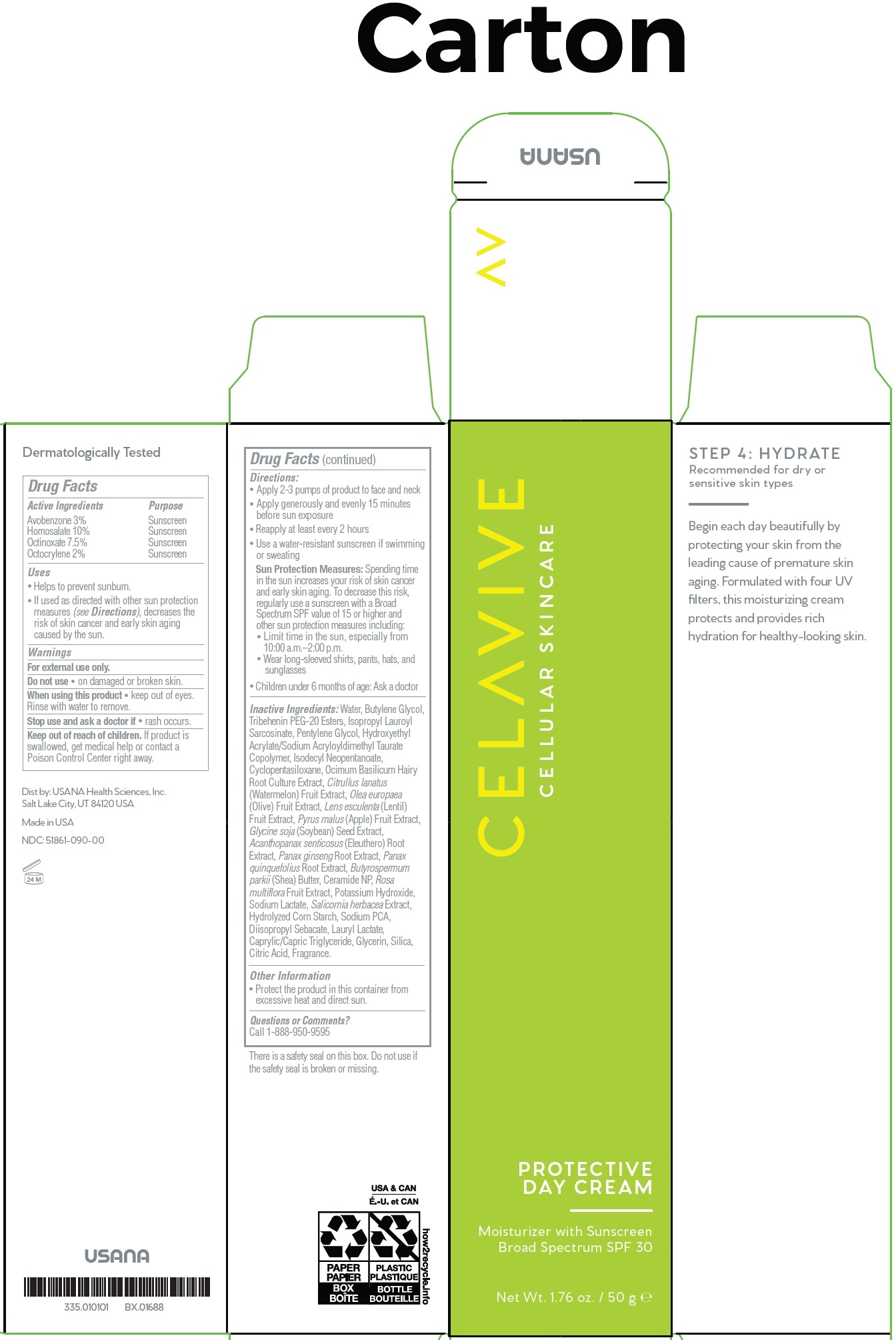 DRUG LABEL: Celavive Protective Day SPF 30
NDC: 51861-091 | Form: CREAM
Manufacturer: USANA Health Sciences, Inc.
Category: otc | Type: HUMAN OTC DRUG LABEL
Date: 20250528

ACTIVE INGREDIENTS: AVOBENZONE 30 mg/1 g; HOMOSALATE 100 mg/1 g; OCTINOXATE 75 mg/1 g; OCTOCRYLENE 20 mg/1 g
INACTIVE INGREDIENTS: WATER; BUTYLENE GLYCOL; TRIBEHENIN PEG-20 ESTERS; ISOPROPYL LAUROYL SARCOSINATE; PENTYLENE GLYCOL; ISODECYL NEOPENTANOATE; CYCLOMETHICONE 5; WATERMELON; BLACK OLIVE; LENTIL; APPLE; SOYBEAN; ELEUTHERO; ASIAN GINSENG; AMERICAN GINSENG; SHEA BUTTER; CERAMIDE NP; ROSA MULTIFLORA FRUIT; POTASSIUM HYDROXIDE; SODIUM LACTATE; SALICORNIA EUROPAEA WHOLE; SODIUM PYRROLIDONE CARBOXYLATE; DIISOPROPYL SEBACATE; LAURYL LACTATE; MEDIUM-CHAIN TRIGLYCERIDES; GLYCERIN; SILICON DIOXIDE; CITRIC ACID MONOHYDRATE

Celavive Protective Day Cream SPF 30

Active Ingredients

Avobenzone 3%

Homosalate 10%

Octinoxate 7.5%

Octocrylene 2%

Purpose

Sunscreen

Uses

• Helps to prevent sunburn.
• If used as directed with other sun protection measures (see Directions), decreases the risk of skin cancer and early skin aging caused by the sun.

Warnings

For external use only.

Do not use

• on damaged or broken skin.

When using this product

• keep out of eyes. Rinse with water to remove.

Stop use and ask a doctor if

• rash occurs.

Keep out of reach of children.

If product is swallowed, get medical help or contact a Poison Control Center right away.

Directions:

• Apply 2-3 pumps of product to face and neck
• Apply generously and evenly 15 minutes before sun exposure
• Reapply at least every 2 hours
• Use a water-resistant sunscreen if swimming or sweating
Sun Protection Measures:Spending time in the sun increases your risk of skin cancer and early skin aging. To decrease this risk, regularly use a sunscreen with a Broad Spectrum SPF value of 15 or higher and other sun protection measures including:
• Limit time in the sun, especially from 10:00 a.m.–2:00 p.m.
• Wear long-sleeved shirts, pants, hats, and sunglasses
• Children under 6 months of age: Ask a doctor

Inactive Ingredients:

Water, Butylene Glycol, Tribehenin PEG-20 Esters, Isopropyl Lauroyl Sarcosinate, Pentylene Glycol, Hydroxyethyl Acrylate/Sodium Acryloyldimethyl Taurate Copolymer, Isodecyl Neopentanoate, Cyclopentasiloxane, Ocimum Basilicum Hairy Root Culture Extract, Citrullus lanatus (Watermelon) Fruit Extract, Olea europaea (Olive) Fruit Extract, Lens esculenta (Lentil) Fruit Extract, Pyrus malus (Apple) Fruit Extract, Glycine soja (Soybean) Seed Extract, Acanthopanax senticosus (Eleuthero) Root Extract, Panax ginseng Root Extract, Panax quinquefolius Root Extract, Butyrospermum parkii (Shea) Butter, Ceramide NP, Rosa multiflora Fruit Extract, Potassium Hydroxide, Sodium Lactate, Salicornia herbacea Extract, Hydrolyzed Corn Starch, Sodium PCA, Diisopropyl Sebacate, Lauryl Lactate, Caprylic/Capric Triglyceride, Glycerin, Silica, Citric Acid, Fragrance.

Other Information

- Protect the product in this container from excessive heat and direct sun.

Questions or Comments?

Call 1-888-950-9595